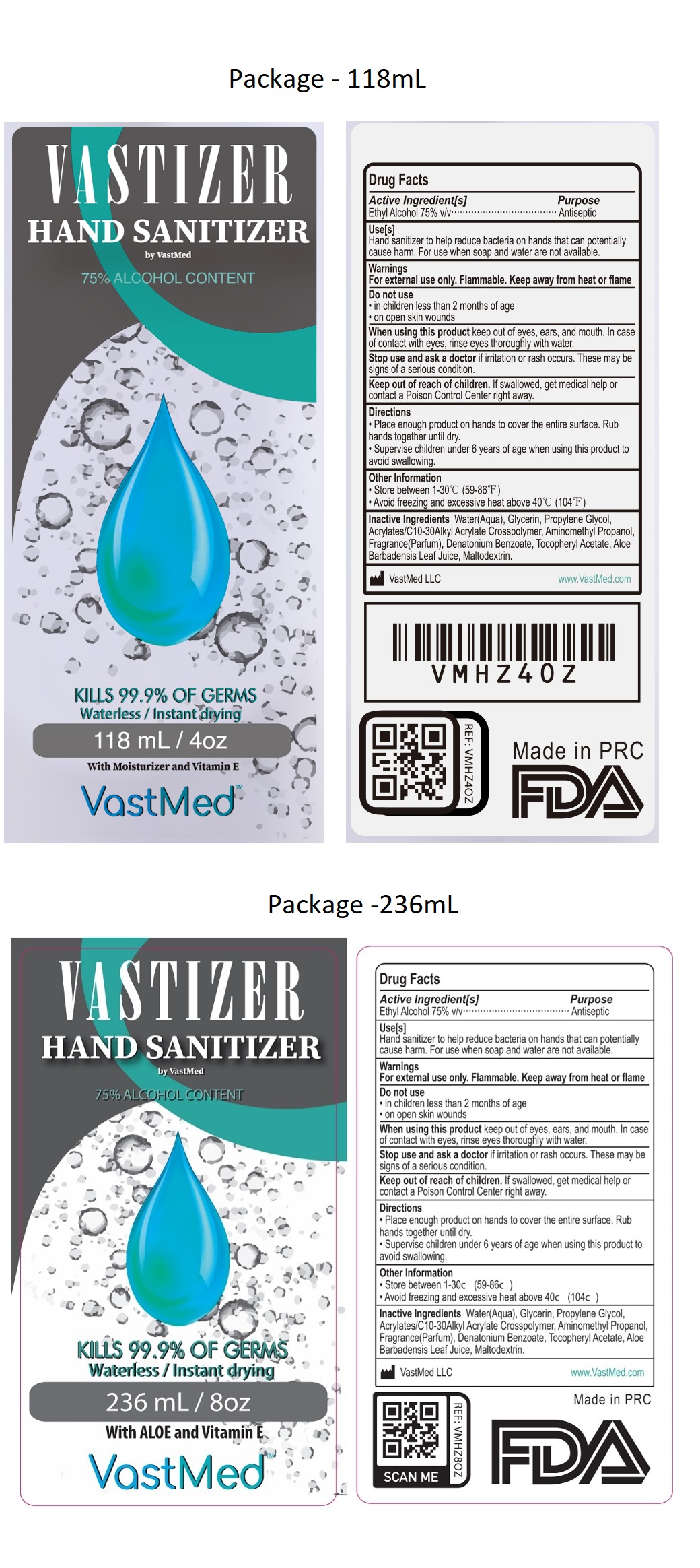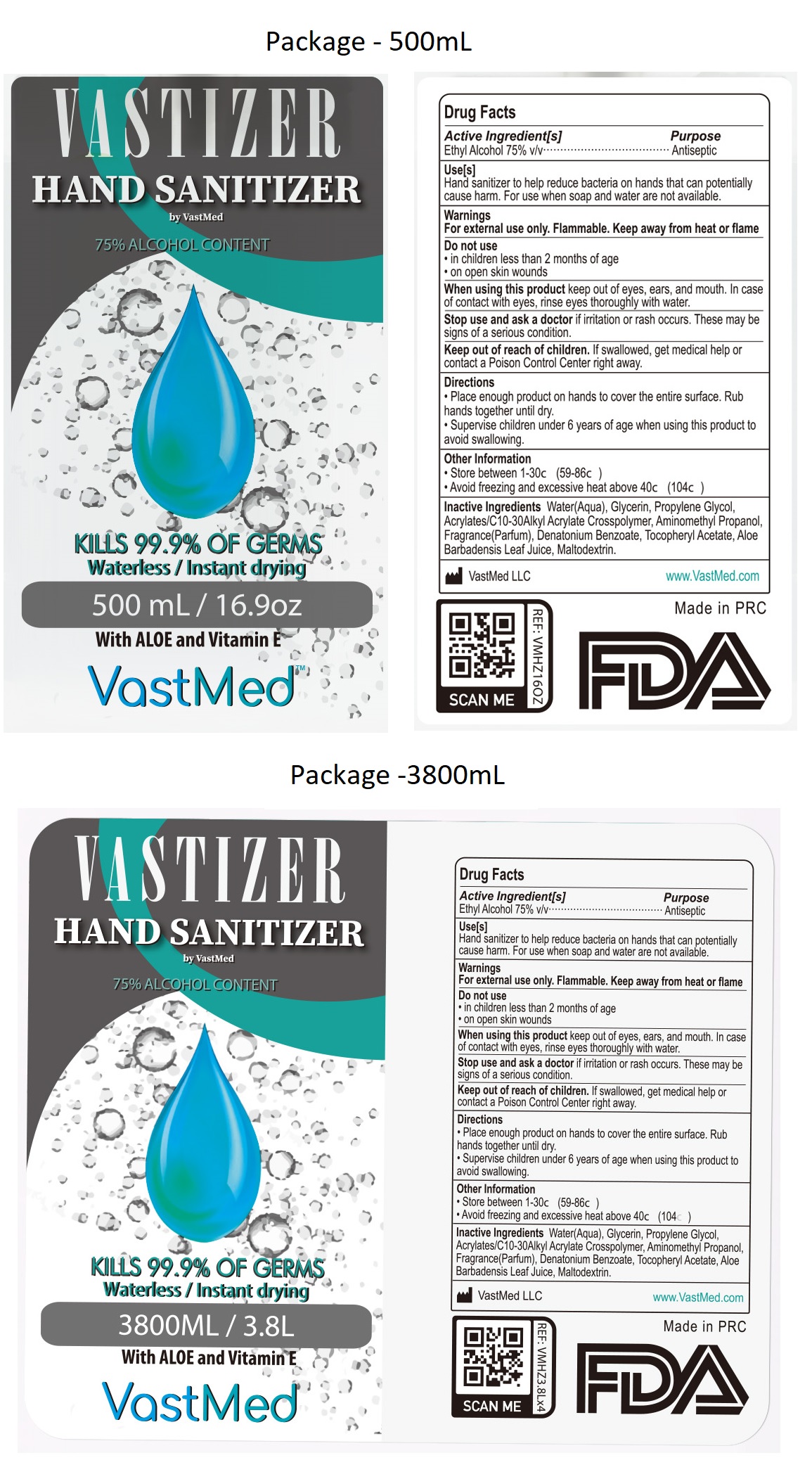 DRUG LABEL: VASTIZER HAND SANITIZER
NDC: 79586-101 | Form: LIQUID
Manufacturer: VastMed LLC
Category: otc | Type: HUMAN OTC DRUG LABEL
Date: 20220509

ACTIVE INGREDIENTS: ALCOHOL 75 mL/100 mL
INACTIVE INGREDIENTS: WATER; GLYCERIN; PROPYLENE GLYCOL; CARBOMER INTERPOLYMER TYPE A (ALLYL SUCROSE CROSSLINKED); AMINOMETHYLPROPANOL; DENATONIUM BENZOATE; .ALPHA.-TOCOPHEROL ACETATE; ALOE VERA LEAF; MALTODEXTRIN

VASTIZER HAND SANITIZER

Active Ingredient[s]

Ethyl Alcohol 75% v/v

Purpose

Antiseptic

Use[s]

Hand sanitizer to help reduce bacteria on hands that can potentially cause harm. For use when soap and water are not available.

Warnings

For external use only. Flammable. Keep away from heat or flame.

Do not use

• in children less than 2 months of age

• on open skin wounds

When using this product keep out of eyes, ears, and mouth. In case of contact with eyes, rinse eyes thoroughly with water.

Stop use and ask a doctor if irritation or rash occurs. These may be signs of a serious condition.

Keep out of reach of children. If swallowed, get medical help or contact a Poison Control Center right away.

Directions

• Place enough product on hands to cover the entire surface. Rub hands together until dry.

• Supervise children under 6 years of age when using this product to avoid swallowing.

Other Information

• Store between 1-30c (59-86c)

• Avoid freezing and excessive heat above 40c (104c)

Inactive Ingredients

Water(Aqua), Glycerin, Propylene Glycol, Acrylates/C10-30Alkyl Acrylate Crosspolymer, Aminomethyl Propanol, Fragrance(Parfum), Denatonium Benzoate, Tocopheryl Acetate, Aloe Barbadensis Leaf Juice, Maltodextrin.

by VastMed

75% ALCOHOL CONTENT

KILLS 99.9% OF GERMS

Waterless / Instant drying

With ALOE and Vitamin E

VastMed LLC www.VastMed.com

Made in PRC